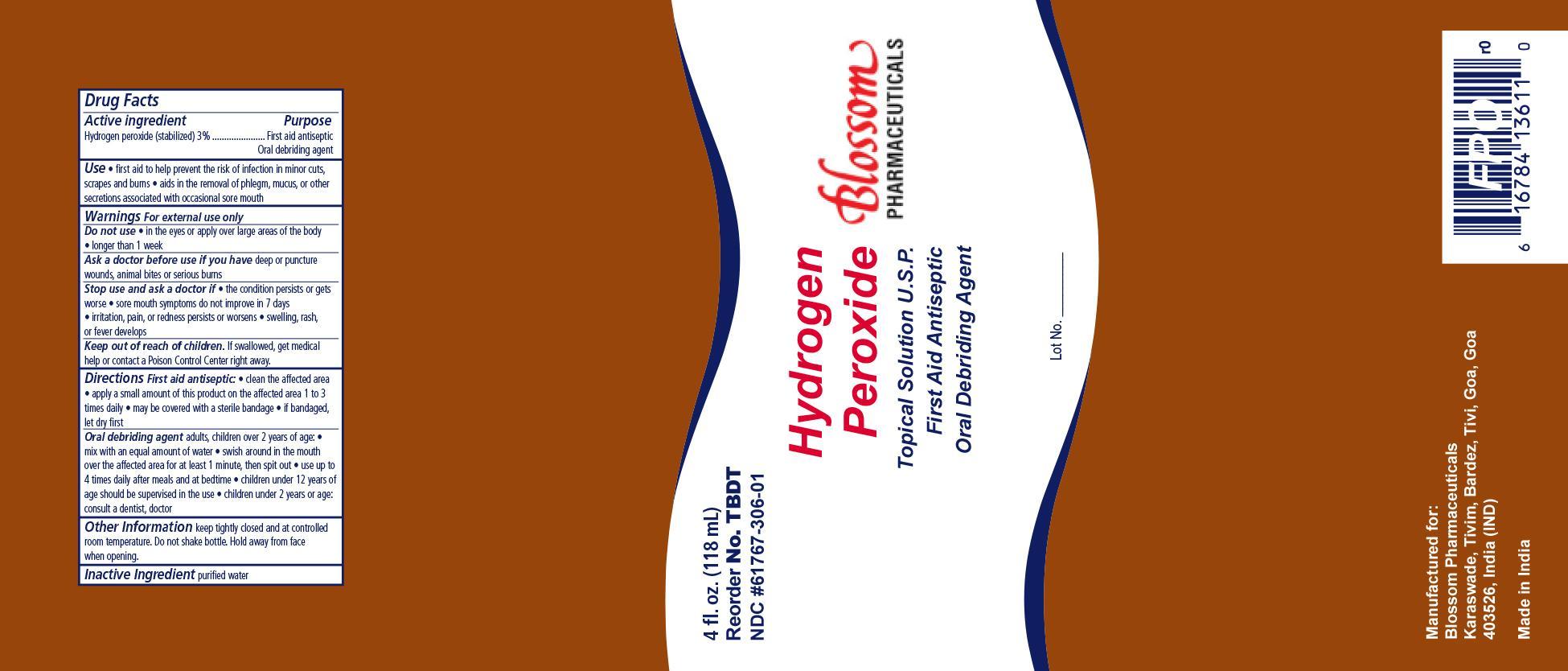 DRUG LABEL: Blossom HP 3
NDC: 61767-306 | Form: LIQUID
Manufacturer: Blossom Pharmaceuticals
Category: otc | Type: HUMAN OTC DRUG LABEL
Date: 20140131

ACTIVE INGREDIENTS: HYDROGEN PEROXIDE 2.65 mL/100 mL
INACTIVE INGREDIENTS: WATER

Hydrogen Peroxide 3%

Active Ingredient Purpose

Hydrogen peroxide 3% v/v Antiseptic

Oral debriding agent

PURPOSE

First aid to help prevent the risk of infection in:

- minor cuts
- scrapes
- burns
- aids in the removal of phlegm, mucus, or other secretions associated with occassional sore mouth.

WARNINGS

- For external use only
- Ask a doctor before use if you have deep puncture wounds, animal bites or serious burns.

- Stop use and ask a doctor if condition persist or gets worse.
- Sore mouth symptoms do not improve in 7 days
- irritation, pain, or redness persists or worsens
- swelling rash or fever develops

INDICATIONS & USAGE

Do not use:

- in the eyes or over large areas of the body
- longer than 1 week

KEEP OUT OF REACH OF CHILDREN

IIf swallowed, get medical help or contact a Poison Control Center right away.

DOSAGE & ADMINISTRATION

DIRECTIONS as a First Aid Antiseptic:

- clean the affected area
- apply a small amount of this product on the affected area 1 to 3 times a day
- may be covered with a sterile bandage
- if bandaged let dry first

DIRECTIONS as a Oral Debriding Agent:

Adults, children over 2 years of age:

- mix with an equal amount of water
- swish around the mouth in the affected area for at least 1 minute, then spit out
- use up to 4 times daily after meals and at bedtime
- children under 12 years of age should be supervised in the use
- children under 2 years of age consult a dentis or doctor

OTHER INFORMATION

- keep tightly closed and at controlled room temperature.
- do not shake bottle
- Hold away from face when opening

INACTIVE INGREDIENT

- Water

PRINCIPAL DISPLAY PANEL

Blossom Pharmaceuticals 3% Hydrogen Peroxide

Hydrogen Peroxide BP.jpg